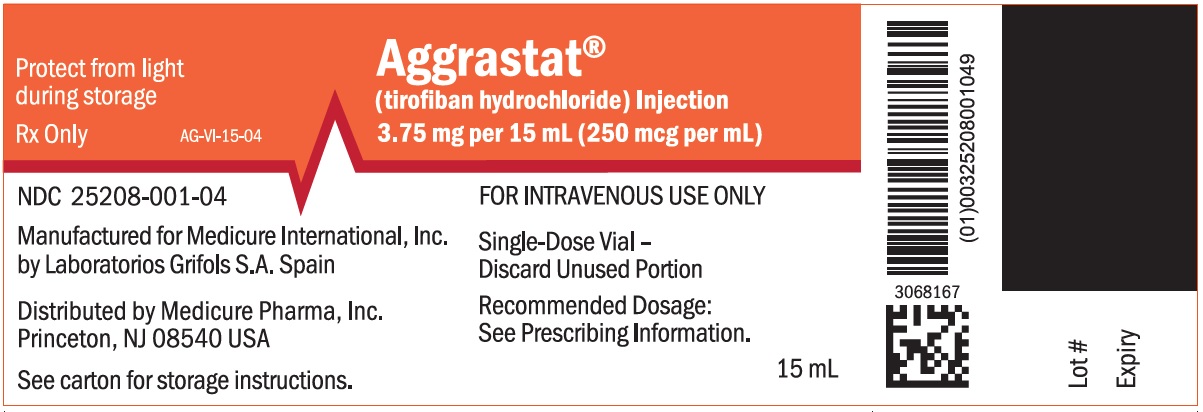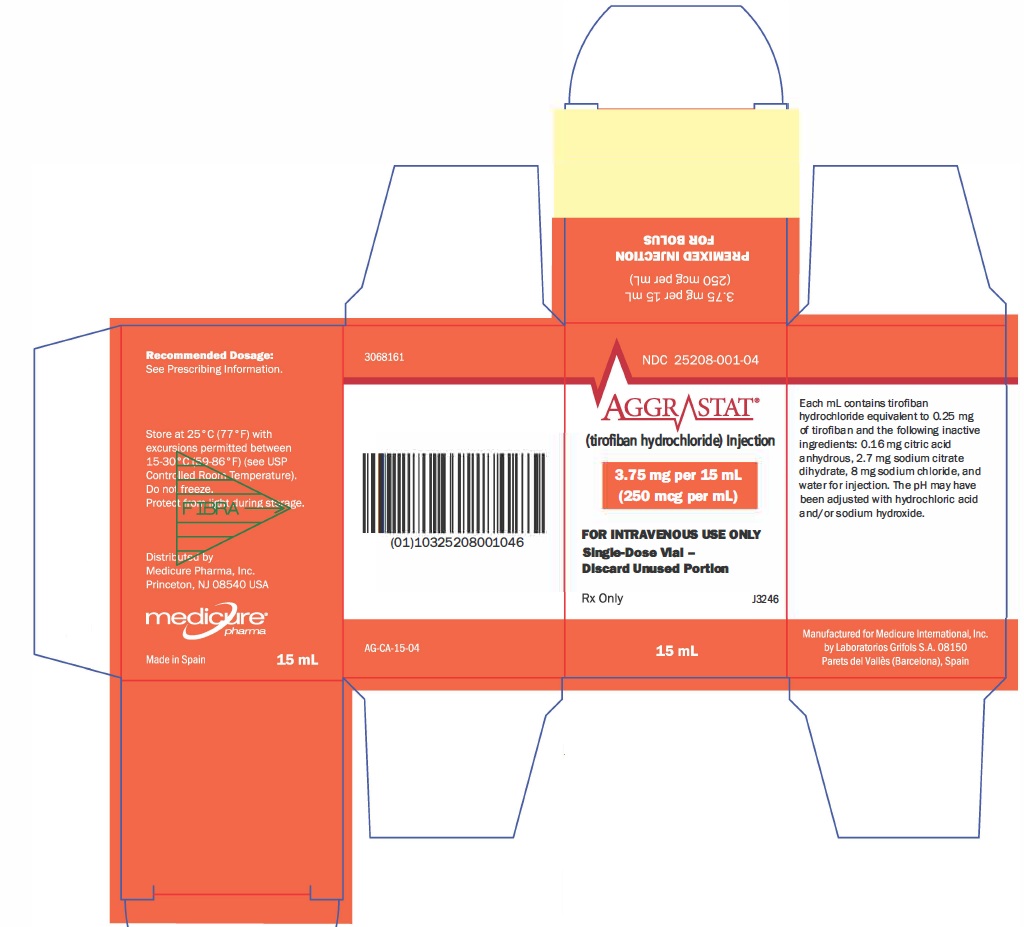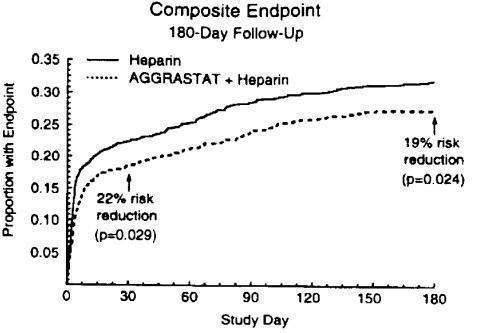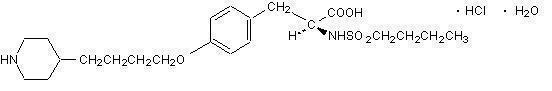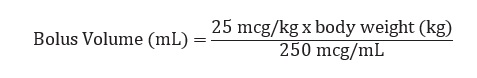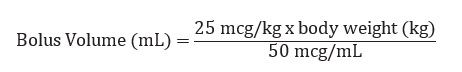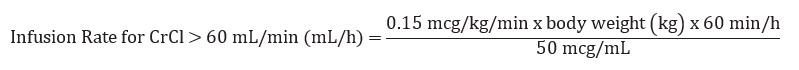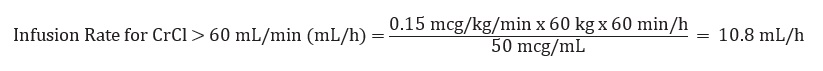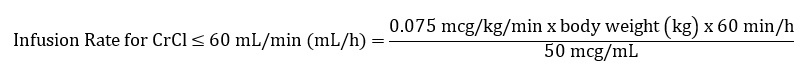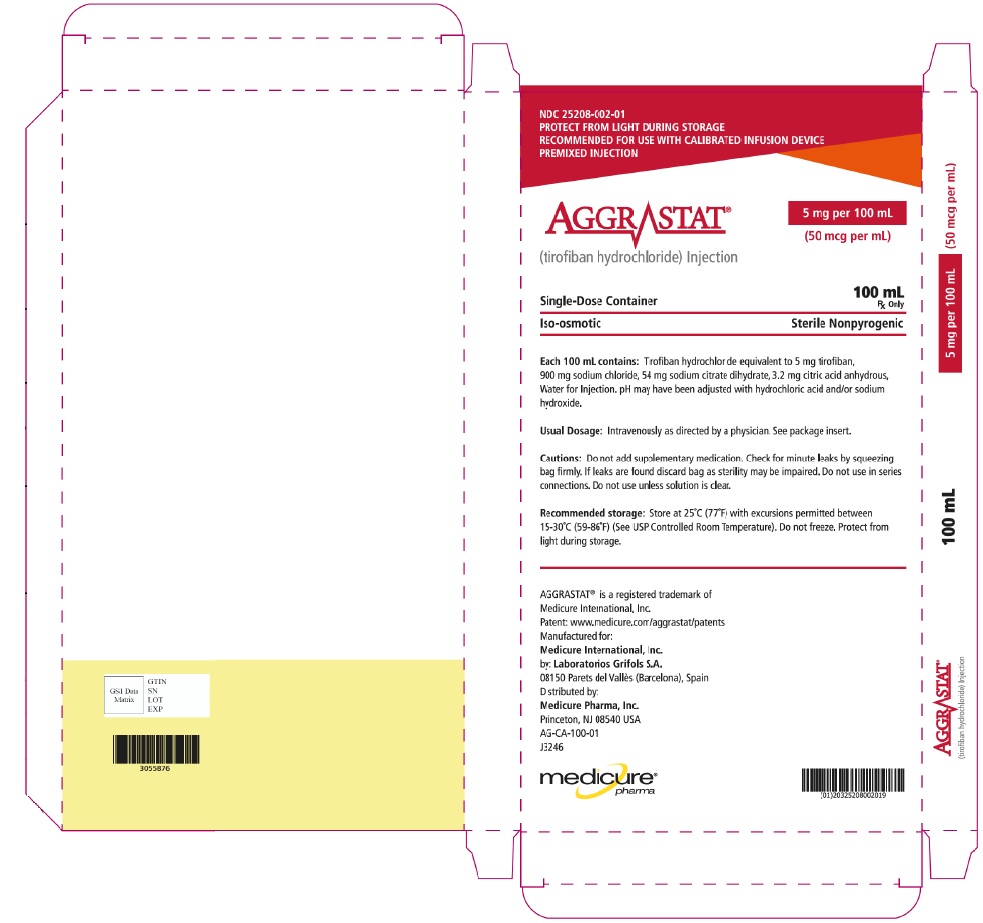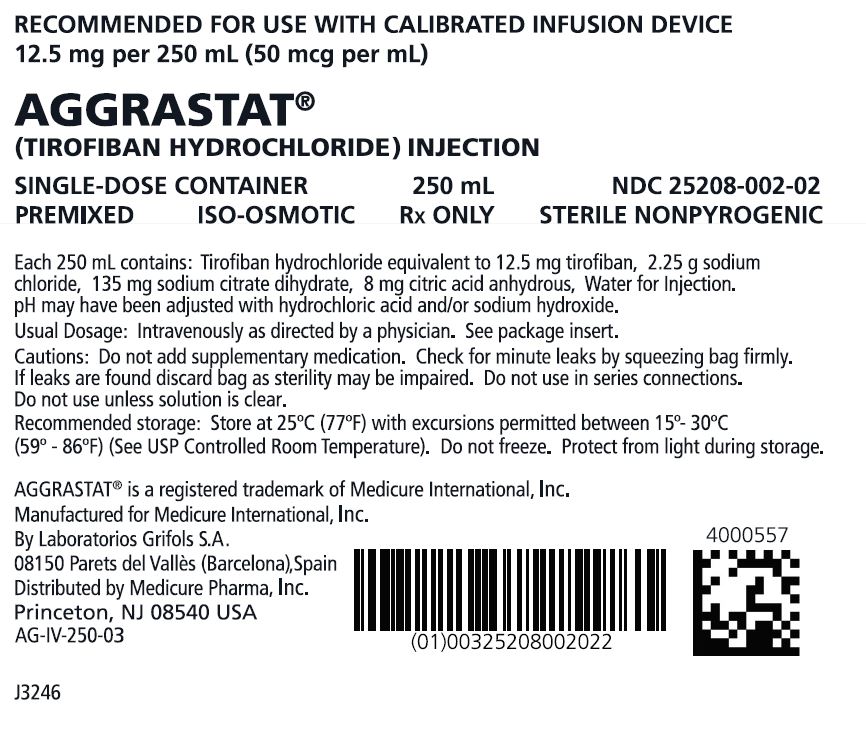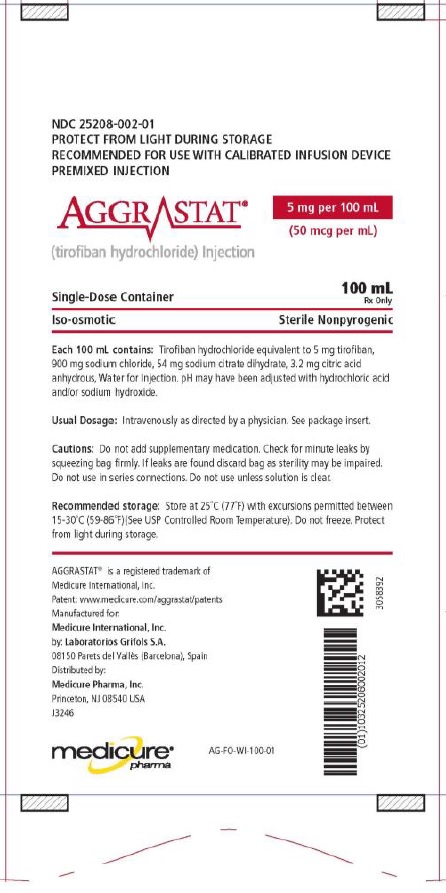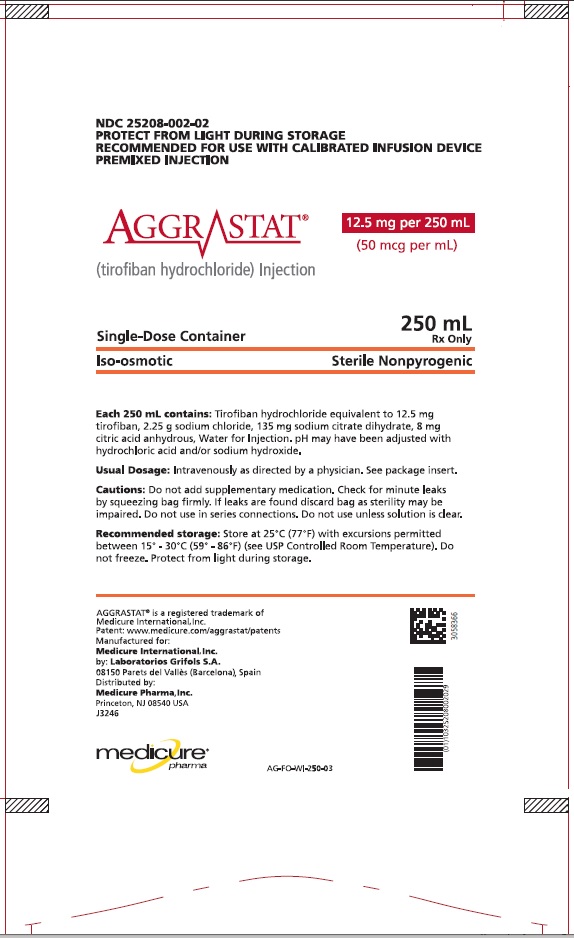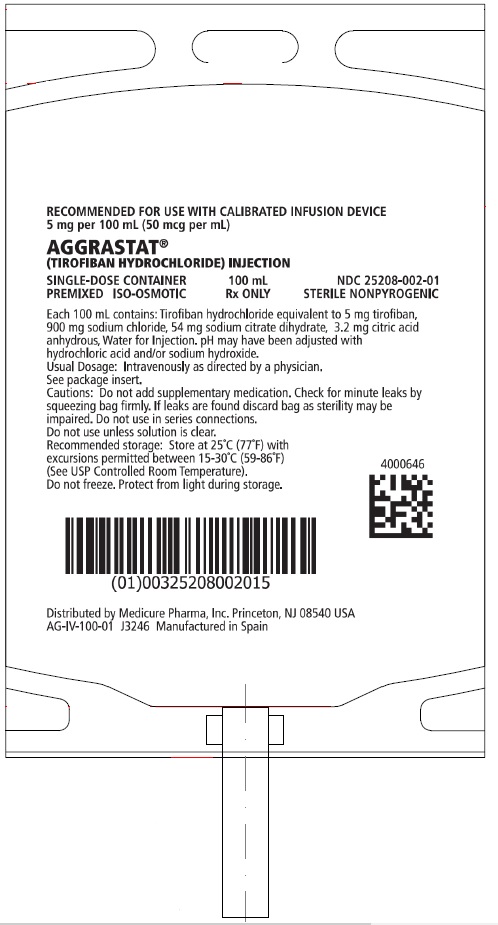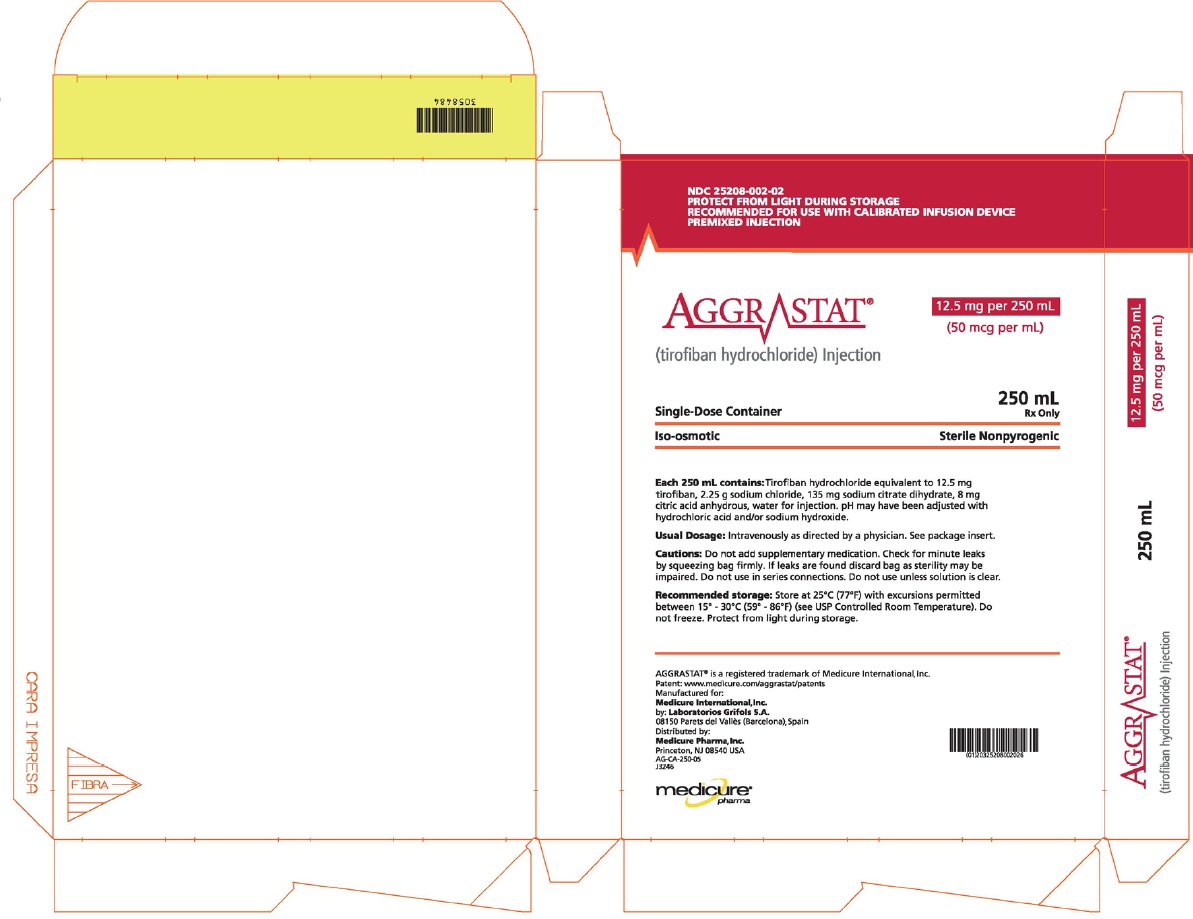 DRUG LABEL: AGGRASTAT
NDC: 25208-002 | Form: INJECTION, SOLUTION
Manufacturer: Medicure International Inc
Category: prescription | Type: HUMAN PRESCRIPTION DRUG LABEL
Date: 20250101

ACTIVE INGREDIENTS: TIROFIBAN HYDROCHLORIDE 5 mg/100 mL
INACTIVE INGREDIENTS: ANHYDROUS CITRIC ACID 3.2 mg/100 mL; TRISODIUM CITRATE DIHYDRATE 54 mg/100 mL; SODIUM CHLORIDE 900 mg/100 mL; WATER

HIGHLIGHTS OF PRESCRIBING INFORMATION

These highlights do not include all the information needed to use AGGRASTAT® (tirofiban hydrochloride) safely and effectively. See full prescribing information for AGGRASTAT.
AGGRASTAT (tirofiban hydrochloride) injection, for intravenous use
Initial U.S. Approval: 1998

1 INDICATIONS AND USAGE

AGGRASTAT is a platelet aggregation inhibitor indicated to reduce the rate of thrombotic cardiovascular events (combined endpoint of death, myocardial infarction, or refractory ischemia/repeat cardiac procedure) in patients with non-ST elevation acute coronary syndrome (NSTE-ACS).

2 DOSAGE AND ADMINISTRATION

- Administer intravenously 25 mcg/kg within 5 minutes and then 0.15 mcg/kg/min for up to 18 hours. In patients with creatinine clearance ≤60 mL/min, give 25 mcg/kg within 5 minutes and then 0.075 mcg/kg/min. (2)

3 DOSAGE FORMS AND STRENGTHS

- Injection: 12.5 mg/250mL (50 mcg/mL) in 250 mL bag (3)
- Injection: 5 mg/100mL (50 mcg/mL) in 100 mL bag. (3)
- Injection: 3.75 mg/15mL (250 mcg/mL) in 15 mL bolus vial (3)

4 CONTRAINDICATIONS

- Known hypersensitivity to any component of AGGRASTAT. (4)
- History of thrombocytopenia with prior exposure to AGGRASTAT. (4)
- Active internal bleeding, or history of bleeding diathesis, major surgical procedure or severe physical trauma within the previous month. (4)

5 WARNINGS AND PRECAUTIONS

- AGGRASTAT can cause serious bleeding. If bleeding cannot be controlled discontinue AGGRASTAT. (5.1)
- Thrombocytopenia: Discontinue AGGRASTAT and heparin. (5.2)

6 ADVERSE REACTIONS

Bleeding is the most commonly reported adverse reaction. (6.1)

To report SUSPECTED ADVERSE REACTIONS, contact Medicure at 1-800-509-0544 or FDA at 1-800-FDA-1088 or www.fda.gov/medwatch.

7 DRUG INTERACTIONS

- Coadministration of fibrinolytics, anticoagulants and antiplatelet agents, increases the risk of bleeding. (7)

8 USE IN SPECIFIC POPULATIONS

- Renal Insufficiency: Reduce the dose in patients with severe renal insufficiency. (8.6)

FULL PRESCRIBING INFORMATION

1 INDICATIONS AND USAGE

AGGRASTAT® is indicated to reduce the rate of thrombotic cardiovascular events (combined endpoint of death, myocardial infarction, or refractory ischemia/repeat cardiac procedure) in patients with non-ST elevation acute coronary syndrome (NSTE-ACS).

2 DOSAGE AND ADMINISTRATION

2.1 Recommended Dosage

The recommended dosage is 25 mcg/kg administered intravenously within 5 minutes and then 0.15 mcg/kg/min for up to 18 hours.

2.2 Administration

For intravenous use only. Parenteral drug products should be inspected visually for particulate matter and discoloration prior to administration whenever solution and container permit.

To open the 100 mL or 250 mL premixed bag, first tear off its foil overpouch. The plastic may be somewhat opaque because of moisture absorption during sterilization; the opacity will diminish gradually. Check for leaks by squeezing the inner bag firmly; if any leaks are found or sterility is suspect then the solution should be discarded. Do not use unless the solution is clear and the seal is intact.

Administration Instructions

1. Withdraw the bolus dose of AGGRASTAT from the 15 mL premixed bolus vial into a syringe. Alternatively, the bolus dose of AGGRASTAT may be administered from the 100 mL or 250 mL premixed bag. Do not dilute. Administer the bolus dose within 5 minutes via a syringe or IV pump. For patients ≥ 167 kg, it is recommended that the bolus dose be administered via syringe from the 15 mL premixed bolus vial, to ensure that delivery time does not exceed 5 minutes.
2. Immediately following the bolus dose administration, administer the maintenance infusion from the 100 mL premixed bag or the 250 mL premixed bag via an IV pump.
3. Discard any unused portion left in the vial or bag.

The recommended bolus volume using the 15 mL premixed bolus vial can be calculated using the following equation:

The recommended bolus volume using the 100 mL premixed bag or 250 mL premixed bag can be calculated using the following equation:

The recommended infusion rate for patients with CrCl (Creatinine Clearance) >60 mL/min using the 100 mL premixed bag or 250 mL premixed bag can be calculated using the following equation:

Example calculation of infusion rate for 60 kg patient with CrCl >60 mL/min using the 100 mL premixed bag or 250 mL premixed bag:

Drug Compatibilities
AGGRASTAT can be administered in the same intravenous line as heparin, atropine sulfate, dobutamine, dopamine, epinephrine hydrochloride (HCl), famotidine injection, furosemide, lidocaine, midazolam HCl, morphine sulfate, nitroglycerin, potassium chloride, and propranolol HCl. Do not administer AGGRASTAT through the same IV line as diazepam. Do not add other drugs or remove solution directly from the bag with a syringe.

2.3 Dose Adjustment for Renal Impairment

The recommended dosage in patients with CrCl ≤60 mL/min (calculated using the Cockcroft-Gault equation with actual body weight) is 25 mcg/kg intravenously within 5 minutes and then 0.075 mcg/kg/min, for up to 18 hours.

The recommended infusion rate for patients with CrCl ≤ 60 mL/min using 100 mL premixed bag or 250 mL premixed bag can be calculated using the following equation:

3 DOSAGE FORMS AND STRENGTHS

AGGRASTAT is a clear, non-preserved, colorless, isosmotic, sterile premixed injection with sodium chloride for tonicity adjustment available in the following presentations:

Table 1 AGGRASTAT Strength and Packaging
Strength | Volume - Packaging
50 mcg/mL | 250 mL - bag
50 mcg/mL | 100 mL - bag
250 mcg/mL | 15 mL - bolus vial

4 CONTRAINDICATIONS

AGGRASTAT is contraindicated in patients with:

- Severe hypersensitivity reaction to AGGRASTAT (i.e., anaphylactic reactions) [see Adverse Reactions (6.2)].
- A history of thrombocytopenia following prior exposure to AGGRASTAT [see Adverse Reactions (6.1)].
- Active internal bleeding or a history of bleeding diathesis, major surgical procedure or severe physical trauma within the previous month [see Adverse Reactions (6.1)].

5 WARNINGS AND PRECAUTIONS

5.1 General Risk of Bleeding

Bleeding is the most common complication encountered during therapy with AGGRASTAT. Most bleeding associated with AGGRASTAT occurs at the arterial access site for cardiac catheterization. Minimize the use of traumatic or potentially traumatic procedures such as arterial and venous punctures, intramuscular injections, nasotracheal intubation, etc.

Concomitant use of fibrinolytics, anticoagulants and antiplatelet drugs increases the risk of bleeding.

5.2 Thrombocytopenia

Profound thrombocytopenia has been reported with AGGRASTAT. Monitor platelet counts beginning about 6 hours after treatment initiation and daily thereafter. If the platelet count decreases to <90,000/mm^3, monitor platelet counts to exclude pseudothrombocytopenia. If thrombocytopenia is confirmed, discontinue AGGRASTAT and heparin. Previous exposure to a glycoprotein (GP) IIb/IIIa receptor antagonist may increase the risk of developing thrombocytopenia [see Adverse Reactions (6.1)].

6 ADVERSE REACTIONS

6.1 Clinical Trial Experience

Because clinical trials are conducted under widely varying conditions, adverse reaction rates observed in the clinical trials of a drug cannot be directly compared to rates in the clinical trials of another drug and may not reflect the rates observed in clinical practice.

In the PRISM (Platelet Receptor Inhibition for Ischemic Syndrome Management), PRISM-PLUS (Platelet Receptor Inhibition for Ischemic Syndrome Management — Patients Limited by Unstable Signs and Symptoms) and RESTORE (Randomized Efficacy Study of Tirofiban for Outcomes and Restenosis) trials, 1946 patients received AGGRASTAT in combination with heparin and 2002 patients received AGGRASTAT alone for about 3 days. Forty-three percent of the population was >65 years of age and approximately 30% of patients were female. In clinical studies with the recommended regimen (25 mcg/kg bolus followed by a 0.15 mcg/kg/min maintenance infusion), AGGRASTAT was administered in combination with aspirin, clopidogrel and heparin or bivalirudin to over 8000 patients for typically ≤24 hours. Approximately 30% of the population was >65 years of age and approximately 25% were female.

Bleeding

PRISM-PLUS Regimen

The incidences of major and minor bleeding using the TIMI criteria in the PRISM-PLUS study are shown below.

Table 2 TIMI Major and Minor Bleeding in PRISM-PLUS
 | PRISM-PLUS; (NSTE-ACS)
Bleeding; (TIMI Criteria) [Major = Hemoglobin drop of >5.0 g/dL with or without an identified site, intracranial hemorrhage, or cardiac tamponade.] [Minor = Hemoglobin drop of >3.0 g/dL with bleeding from a known site, spontaneous gross hematuria, hematemesis or hemoptysis.] | AGGRASTAT [0.4 mcg/kg/min initial infusion; 0.10 mcg/kg/min maintenance infusion.] + Heparin; (n=773) | Heparin alone; (n=797)
Major Bleeding | 1.4% | 0.8%
Minor Bleeding | 10.5% | 8.0%
Transfusions | 4.0% | 2.8%

The incidence rates of TIMI major bleeding in patients undergoing percutaneous procedures in PRISM-PLUS are shown below.

Table 3 TIMI Major Bleeding Associated with Percutaneous Procedures in PRISM-PLUS
 | AGGRASTAT +; Heparin |  | Heparin alone
 | N | % | N | %
Prior to Procedures | 773 | 0.3 | 797 | 0.1
Following Angiography | 697 | 1.3 | 708 | 0.7
Following PTCA | 239 | 2.5 | 236 | 2.2

The incidence rates of TIMI major bleeding in patients undergoing coronary artery bypass graft surgery (CABG) in PRISM-PLUS within one day of discontinuation of AGGRASTAT were 17% on AGGRASTAT plus heparin (N=29) and 35% on heparin alone (N=31).

Recommended (“High-Dose Bolus”) Regimen

Rates of major bleeds (including any intracranial, intraocular or retroperitoneal hemorrhage, clinically overt signs of hemorrhage associated with a drop in hemoglobin of >3 g/dL or any drop in hemoglobin by 4 g/dL, bleeding requiring transfusion of ≥ 2 U blood products, bleeding directly resulting in death within 7 days or hemodynamic compromise requiring intervention) were consistent with the rates observed in subjects administered the PRISM-PLUS regimen of AGGRASTAT. There was a trend toward greater bleeding in ST segment elevation myocardial infarction (STEMI) patients treated with fibrinolytics prior to administration of AGGRASTAT using the recommended regimen during rescue PCI.

Non-Bleeding

The incidences of non-bleeding adverse events that occurred at an incidence of >1% and numerically higher than control, regardless of drug relationship, are shown below:

Table 4 Non-bleeding Adverse Reactions in PRISM-PLUS
 | AGGRASTAT + Heparin; (N=1953); % | Heparin alone; (N=1887); %
Body as a Whole
Edema/swelling | 2 | 1
Pain, pelvic | 6 | 5
Reaction, vasovagal | 2 | 1
Cardiovascular System
Bradycardia | 4 | 3
Dissection, coronary artery | 5 | 4
Musculoskeletal System
Pain, leg | 3 | 2
Nervous System/Psychiatric
Dizziness | 3 | 2
Skin and Skin Appendage
Sweating | 2 | 1

Thrombocytopenia

Patients treated with AGGRASTAT plus heparin, were more likely to experience decreases in platelet counts than were those on heparin alone. These decreases were reversible upon discontinuation of AGGRASTAT. The percentage of patients with a decrease of platelets to <90,000/mm^3 was 1.5%, compared with 0.6% in the patients who received heparin alone. The percentage of patients with a decrease of platelets to <50,000/mm^3 was 0.3%, compared with 0.1% of the patients who received heparin alone.

6.2 Post-Marketing Experience

The following additional adverse reactions have been identified during post-approval use of AGGRASTAT. Because these reactions are reported voluntarily from a population of uncertain size, it is not always possible to reliably estimate their frequency or establish a causal relationship to the drug exposure.

Hypersensitivity: Severe allergic reactions including anaphylactic reactions have occurred during the first day of AGGRASTAT infusion, during initial treatment, and during readministration of AGGRASTAT. Some cases have been associated with severe thrombocytopenia (platelet counts <10,000/mm^3). No information is available on the formation of antibodies to tirofiban.

7 DRUG INTERACTIONS

Concomitant use of fibrinolytics, anticoagulants and antiplatelet drugs increases the risk of bleeding.

8 USE IN SPECIFIC POPULATIONS

8.1 Pregnancy

Risk Summary
While published data cannot definitively establish the absence of risk, available published case reports have not established an association with tirofiban use during pregnancy and major birth defects, miscarriage, or adverse maternal or fetal outcomes. Untreated myocardial infarction can be fatal to the pregnant woman and fetus (see Clinical Considerations). Studies with tirofiban HCl at intravenous doses up to 5 mg/kg/day (about 5 and 13 times the maximum recommended daily human dose for rat and rabbit, respectively, when compared on a body surface area basis) have revealed no harm to the fetus.

The estimated background risk of major birth defects and miscarriage for the indicated population is unknown. All pregnancies have a background risk of birth defect, loss, or other adverse outcomes. In the U.S. general population, the estimated background risk of major birth defects and miscarriage in clinically recognized pregnancies is 2–4% and 15–20%, respectively.

Clinical Considerations
Disease-associated maternal and/or embryo/fetal risk
Myocardial infarction is a medical emergency in pregnancy which can be fatal to the pregnant woman and fetus if left untreated.

Data
Animal Data
There was no evidence of maternal or developmental toxicity in any of the studies in Table 5.

Table 5 Developmental Toxicity Studies
Type of Study | Species | Dose/Exposure [5 mg/kg/day is ~5 and 13 times the maximum recommended daily human dose for rat and rabbit, respectively, when compared on a body surface area basis.] | Duration/Timing Exposure
(1) Range-finding | Rat; (N=30) | 1, 2, 5 mg/kg/day IV; (N=10 per group) | Once daily from GD 6 through LD 20
(2) Developmental Toxicity | Rat; (N=66) | 1, 2, 5 mg/kg/day IV; (N=22 per group) | Once daily from GD 6 through GD 20
(3) Developmental Toxicity with Postweaning Evaluation | Rat; (N=66) | 1, 2, 5 mg/kg/day IV; (N=22 per group) | Once daily from GD 6 through LD 20
(4) Range-finding (non-pregnant) | Rabbit; (N=21) | 1, 2, 5 mg/kg/day IV; (N=7 per group) | Once daily for 14 days
(5) Range-finding (pregnant) | Rabbit (N=30) | 1, 2, 5 mg/kg/day IV; (N=10 per group) | Once daily from GD 7 through GD 20
(6) Developmental Toxicity | Rabbit; (N=60) | 1, 2, 5 mg/kg/day; (N=20 per group) IV | Once daily from GD 7 through GD 20

8.2 Lactation

Risk Summary
There is no data on the presence of tirofiban in human milk, the effects of the drug on the breastfed infant, or the effects of the drug on human milk production. However, tirofiban is present in rat milk. The developmental and health benefits of breastfeeding should be considered along with the mother’s clinical need for AGGRASTAT and any potential adverse effects on the breastfed child from AGGRASTAT or from the underlying maternal condition.

8.4 Pediatric Use

Safety and effectiveness in pediatric patients have not been established.

8.5 Geriatric Use

Of the total number of patients in controlled clinical studies of AGGRASTAT, 43% were 65 years and over, while 12% were 75 years and over. With respect to efficacy, the effect of AGGRASTAT in the elderly (≥65 years) appeared similar to that seen in younger patients (<65 years). Elderly patients receiving AGGRASTAT with heparin or heparin alone had a higher incidence of bleeding complications than did younger patients, but the incremental risk of bleeding in patients treated with AGGRASTAT in combination with heparin compared to the risk in patients treated with heparin alone was similar regardless of age. No dose adjustment is recommended for the elderly population [see Dosage and Administration (2)].

8.6 Renal Insufficiency

Patients with moderate to severe renal insufficiency have decreased plasma clearance of AGGRASTAT. Reduce the dosage of AGGRASTAT in patients with severe renal insufficiency [see Dosage and Administration (2.3) and Clinical Pharmacology (12.3)].

Safety and efficacy of AGGRASTAT has not been established in patients on hemodialysis.

10 OVERDOSAGE

In clinical trials, inadvertent overdosage with AGGRASTAT occurred in doses up to 2 times the recommended dose for initial infusion doses. Inadvertent overdosage occurred in doses up to 9.8 times the 0.15 mcg/kg/min maintenance infusion rate.

The most frequently reported manifestation of overdosage was bleeding, primarily minor mucocutaneous bleeding events and minor bleeding at the sites of cardiac catheterization [see Warnings and Precautions (5.1)].

Overdosage of AGGRASTAT should be treated by assessment of the patient’s clinical condition and cessation or adjustment of the drug infusion as appropriate.

AGGRASTAT can be removed by hemodialysis.

11 DESCRIPTION

AGGRASTAT contains tirofiban hydrochloride, a non-peptide antagonist of the platelet GP IIb/IIIa receptor, which inhibits platelet aggregation.

Tirofiban hydrochloride monohydrate is chemically described as N-(butylsulfonyl)-O-[4-(4-piperidinyl)butyl]-L-tyrosine monohydrochloride monohydrate.

Its molecular formula is C22H36N2O5S•HCl•H2O and its structural formula is:

Tirofiban hydrochloride monohydrate is a white to off-white, non-hygroscopic, free-flowing powder, with a molecular weight of 495.08. It is very slightly soluble in water.

AGGRASTAT Injection Premixed is supplied as a sterile solution in water for injection, for intravenous use. The pH of the solution ranges from 5.5 to 6.5 adjusted with hydrochloric acid and/or sodium hydroxide.

Each 100 mL of the premixed, isosmotic intravenous injection contains 5.618 mg tirofiban hydrochloride monohydrate equivalent to 5 mg tirofiban (50 mcg/mL) and the following inactive ingredients: 0.9 g sodium chloride, 54 mg sodium citrate dihydrate, and 3.2 mg citric acid anhydrous.

Each 250 mL of the premixed, isosmotic intravenous injection contains 14.045 mg tirofiban hydrochloride monohydrate equivalent to 12.5 mg tirofiban (50 mcg/mL) and the following inactive ingredients: 2.25 g sodium chloride, 135 mg sodium citrate dihydrate, and 8 mg citric acid anhydrous.

AGGRASTAT Injection Premixed Bolus Vial is supplied as a sterile, isosmotic, concentrated solution for intravenous bolus injection, in 15 mL vials. No dilution is required. Each 15 mL of the premixed, isosmotic intravenous injection bolus vial contains 4.215 mg of tirofiban hydrochloride monohydrate equivalent to 3.75 mg of tirofiban and the following inactive ingredients: 120 mg sodium chloride, 40.5 mg sodium citrate dihydrate, and 2.4 mg citric acid anhydrous and water for injection.

12 CLINICAL PHARMACOLOGY

12.1 Mechanism of Action

AGGRASTAT is a reversible antagonist of fibrinogen binding to the GP IIb/IIIa receptor, the major platelet surface receptor involved in platelet aggregation. When administered intravenously, AGGRASTAT inhibits ex vivo platelet aggregation in a dose- and concentration-dependent manner.

When given according to the PRISM-PLUS regimen of 0.4 mcg/kg/min over 30 minutes followed by a 0.1 mcg/kg/min maintenance infusion, >90% inhibition of platelet aggregation is attained by the end of the 30-minute infusion. When given according to the recommended regimen of 25 mcg/kg followed by a 0.15 mcg/kg/min maintenance infusion, >90% inhibition of platelet aggregation is attained within 10 minutes. Platelet aggregation inhibition is reversible following cessation of the infusion of AGGRASTAT.

12.2 Pharmacodynamics

AGGRASTAT inhibits platelet function, as demonstrated by its ability to inhibit ex vivo adenosine phosphate (ADP)-induced platelet aggregation and prolong bleeding time in healthy subjects and patients with coronary artery disease. The time course of inhibition parallels the plasma concentration profile of the drug.

Following discontinuation of an infusion of AGGRASTAT 0.10 mcg/kg/min, ex vivo platelet aggregation returns to near baseline in 4 to 8 hours in approximately 90% of patients with coronary artery disease. The addition of heparin to this regimen does not significantly alter the percentage of subjects with >70% inhibition of platelet aggregation (IPA), but does increase the average bleeding time, as well as the number of patients with bleeding times prolonged to >30 minutes. Similar platelet aggregation recovery rates are observed following discontinuation of a 0.15 mcg/kg/min infusion.

12.3 Pharmacokinetics

Tirofiban has a half-life of approximately 2 hours. It is cleared from the plasma largely by renal excretion, with about 65% of an administered dose appearing in urine and about 25% in feces, both largely as unchanged tirofiban. Metabolism appears to be limited.

Tirofiban is not highly bound to plasma proteins and protein binding is concentration independent over the range of 0.01 to 25 mcg/mL. The unbound fraction in human plasma is 35%. The steady state volume of distribution of tirofiban ranges from 22 to 42 liters.

In healthy subjects, the plasma clearance of tirofiban ranges from 213 to 314 mL/min. Renal clearance accounts for 39 to 69% of plasma clearance.

Specific Populations

There is no effect on clearance of tirofiban by sex, race, age, or hepatic impairment.

Renal Insufficiency

Plasma clearance of tirofiban is decreased about 40% in subjects with creatinine clearance <60 mL/min and >50% in patients with creatinine clearance <30 mL/min, including patients requiring hemodialysis [see Dosage and Administration (2.3)]. Tirofiban is removed by hemodialysis.

13 NONCLINICAL TOXICOLOGY

13.1 Carcinogenesis, Mutagenesis, Impairment of Fertility

The carcinogenic potential of AGGRASTAT has not been evaluated.

Tirofiban HCl was negative in the in vitro microbial mutagenesis and V-79 mammalian cell mutagenesis assays. In addition, there was no evidence of direct genotoxicity in the in vitro alkaline elution and in vitro chromosomal aberration assays. There was no induction of chromosomal aberrations in bone marrow cells of male mice after the administration of intravenous doses up to 5 mg tirofiban/kg (about 3 times the maximum recommended daily human dose when compared on a body surface area basis).

Fertility and reproductive performance were not affected in studies with male and female rats given intravenous doses of tirofiban up to 5 mg/kg/day (about 5 times the maximum recommended daily human dose when compared on a body surface area basis).

14 CLINICAL STUDIES

Two large-scale clinical studies established the efficacy of AGGRASTAT in the treatment of patients with NSTE-ACS (unstable angina/non-ST elevation MI). The two studies examined AGGRASTAT alone and added to heparin, prior to and after percutaneous coronary revascularization (if indicated) (PRISM-PLUS) and in comparison to heparin in a similar population (PRISM). These trials are discussed in detail below.

PRISM-PLUS (Platelet Receptor Inhibition for Ischemic Syndrome Management — Patients Limited by Unstable Signs and Symptoms)

In the double-blind PRISM-PLUS trial, 1570 patients with documented NSTE-ACS within 12 hours of entry into the study were randomized to AGGRASTAT (30 minute initial infusion of 0.4 mcg/kg/min followed by a maintenance infusion of 0.10 mcg/kg/min) in combination with heparin (bolus of 5,000 U followed by an infusion of 1,000 U/h titrated to maintain an activated partial thromboplastin time (APTT) of approximately 2 times control) or to heparin alone. All patients received concomitant aspirin unless contraindicated. Patients who were medically managed or who underwent revascularization procedures were studied. Patients underwent 48 hours of medical stabilization on study drug therapy, and they were to undergo angiography before 96 hours (and, if indicated, angioplasty/atherectomy, while continuing on AGGRASTAT and heparin for 12-24 hours after the procedure). AGGRASTAT and heparin could be continued for up to 108 hours. Exclusions included contraindications to anticoagulation, decompensated heart failure, platelet count <150,000/mm^3, and serum creatinine >2.5 mg/dL. The mean age of the population was 63 years; 32% of patients were female and approximately half of the population presented with non-ST elevation myocardial infarction. On average, patients received AGGRASTAT for 71 hours.

A third group of patients was initially randomized to AGGRASTAT alone (no heparin). This arm was stopped when the group was found, at an interim look, to have greater mortality than the other two groups.

The primary endpoint of the study was a composite of refractory ischemia, new MI and death within 7 days. There was a 32% risk reduction in the overall composite primary endpoint. The components of the composite were examined separately and the results are shown in Table 6. Note that the sum of the individual components may be greater than the composite (if a patient experiences multiple component events only one event counts towards the composite).

Table 6 Primary Outcomes at 7 days in PRISM-PLUS
Endpoint | AGGRASTAT+; Heparin; (n=773) | Heparin; (n=797) | Risk Reduction | p-value
Death, new MI, and refractory ischemia at 7 days | 12.9% | 17.9% | 32% | 0.004
Death | 1.9% | 1.9% | --- | ---
MI | 3.9% | 7.0% | 47% | 0.006
Refractory Ischemia | 9.3% | 12.7% | 30% | 0.023

The benefit seen at 7 days was maintained over time. The risk reduction in the composite endpoint at 30 days and 6 months is shown in the Kaplan-Meier curve below.

Figure 1. Time to first event of death, new MI, or refractory ischemia in PRISM-PLUS

An analysis of the results by sex suggests that women who are medically managed or who undergo subsequent percutaneous transluminal coronary angioplasty (PTCA)/atherectomy may receive less benefit from AGGRASTAT (95% confidence limits for relative risk of 0.61-1.74) than do men (0.43-0.89) (p=0.11). This difference may be a true treatment difference, the effect of other differences in these subgroups, or a chance occurrence.

Approximately 90% of patients in the PRISM-PLUS study underwent coronary angiography and 30% underwent angioplasty/atherectomy during the first 30 days of the study. The majority of these patients continued on study drug throughout these procedures. AGGRASTAT was continued for 12-24 hours (average 15 hours) after angioplasty/atherectomy. The effects of AGGRASTAT at Day 30 did not appear to differ among sub-populations that did or did not receive PTCA or CABG, both prior to and after the procedure.

PRISM (Platelet Receptor Inhibition for Ischemic Syndrome Management)

In the PRISM study, a randomized, parallel, double-blind study, 3232 patients with NSTE-ACS intended to be managed without coronary intervention were randomized to AGGRASTAT (initial dose of 0.6 mcg/kg/min for 30 minutes followed by 0.15 mcg/kg/min for 47.5 hours) or heparin (5000-unit intravenous bolus followed by an infusion of 1000 U/h for 48 hours). The mean age of the population was 62 years; 32% of the population was female and 25% had non-ST elevation MI on presentation. Thirty percent had no ECG evidence of cardiac ischemia. Exclusion criteria were similar to PRISM-PLUS. The primary endpoint was the composite endpoint of refractory ischemia, MI or death at the end of the 48-hour drug infusion. The results are shown in Table 7.

Table 7 Primary Outcomes in PRISM – Cardiac Ischemia Events
Composite Endpoint (death, MI, or refractory ischemia) | AGGRASTAT; (n=1616) | Heparin; (n=1616) | Risk Reduction | p-value
2 Days (end of drug infusion) | 3.8% | 5.6% | 33% | 0.015
7 Days | 10.3% | 11.3% | 10% | 0.33

In the PRISM study, no adverse effect of AGGRASTAT on mortality at either 7 or 30 days was detected. This result is different from that in the PRISM-PLUS study, where the arm that included AGGRASTAT without heparin (N=345) was dropped at an interim analysis by the Data Safety Monitoring Committee for increased mortality at 7 days.

16 HOW SUPPLIED/STORAGE AND HANDLING

AGGRASTAT is supplied as a clear, non-preserved, colorless, isosmotic, sterile premixed solution with sodium chloride for tonicity adjustment.

Table 8 AGGRASTAT Product Details
Strength | Total Amount | Packaging | NDC #
50 mcg/mL | 12.5 mg/250 mL | bag | 25208-002-02
50 mcg/mL | 5 mg/100 mL | bag | 25208-002-01
250 mcg/mL | 3.75 mg/15 mL | bolus vial | 25208-001-04

FOR INTRAVENOUS USE ONLY

Store AGGRASTAT at controlled room temperature, 25°C (77°F) with excursions permitted between 15-30°C (59-86°F) [see USP Controlled Room Temperature]. Do not freeze. Protect from light during storage.

17 PATIENT COUNSELING INFORMATION

Advise patients to watch closely for any signs of bleeding or bruising and to report these to their health care provider when they occur.

Advise patients to discuss with their health care provider their use of any other medications, including over-the-counter or herbal products prior to AGGRASTAT use.

Patent: www.medicure.com/aggrastat/patents

AGGRASTAT is manufactured for:

MEDICURE INTERNATIONAL, INC.

by:

EMERGENT BIOSOLUTIONS

Baltimore, Maryland 21230 USA

And

LABORATORIOS GRIFOLS S.A

08150 Parets del Vallès (Barcelona), Spain

Distributed by:

MEDICURE PHARMA, INC.
Princeton, NJ 08540 USA
1-800-509-0544

PIM-11

* Registered trademark of Medicure International, Inc.
© 2024
Copyright used under license.
All rights reserved.

Label 12.5 mg/250 mL - Bag

PACKAGE LABEL

Container 12.5 mg/250 mL - Bag

PACKAGE LABEL

Carton